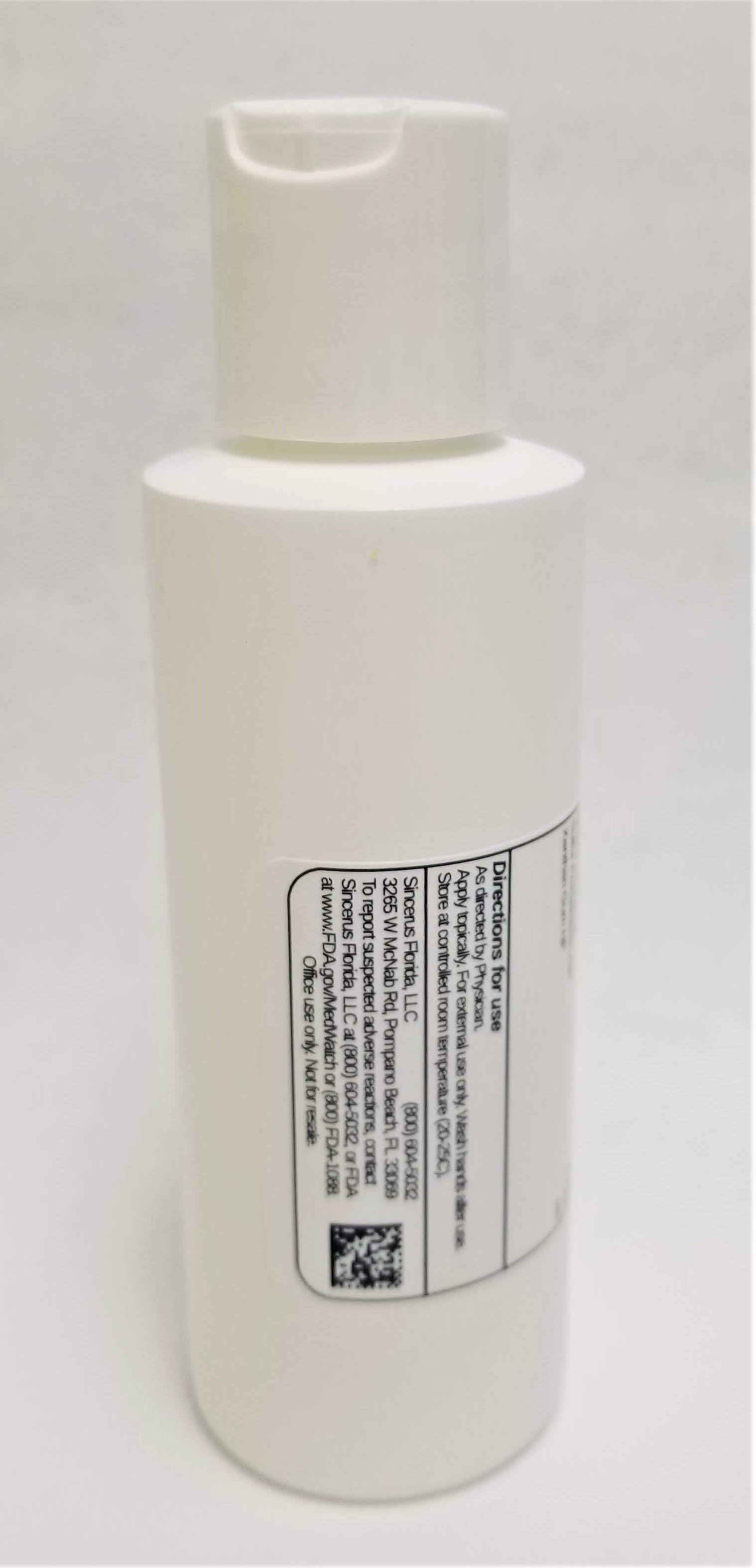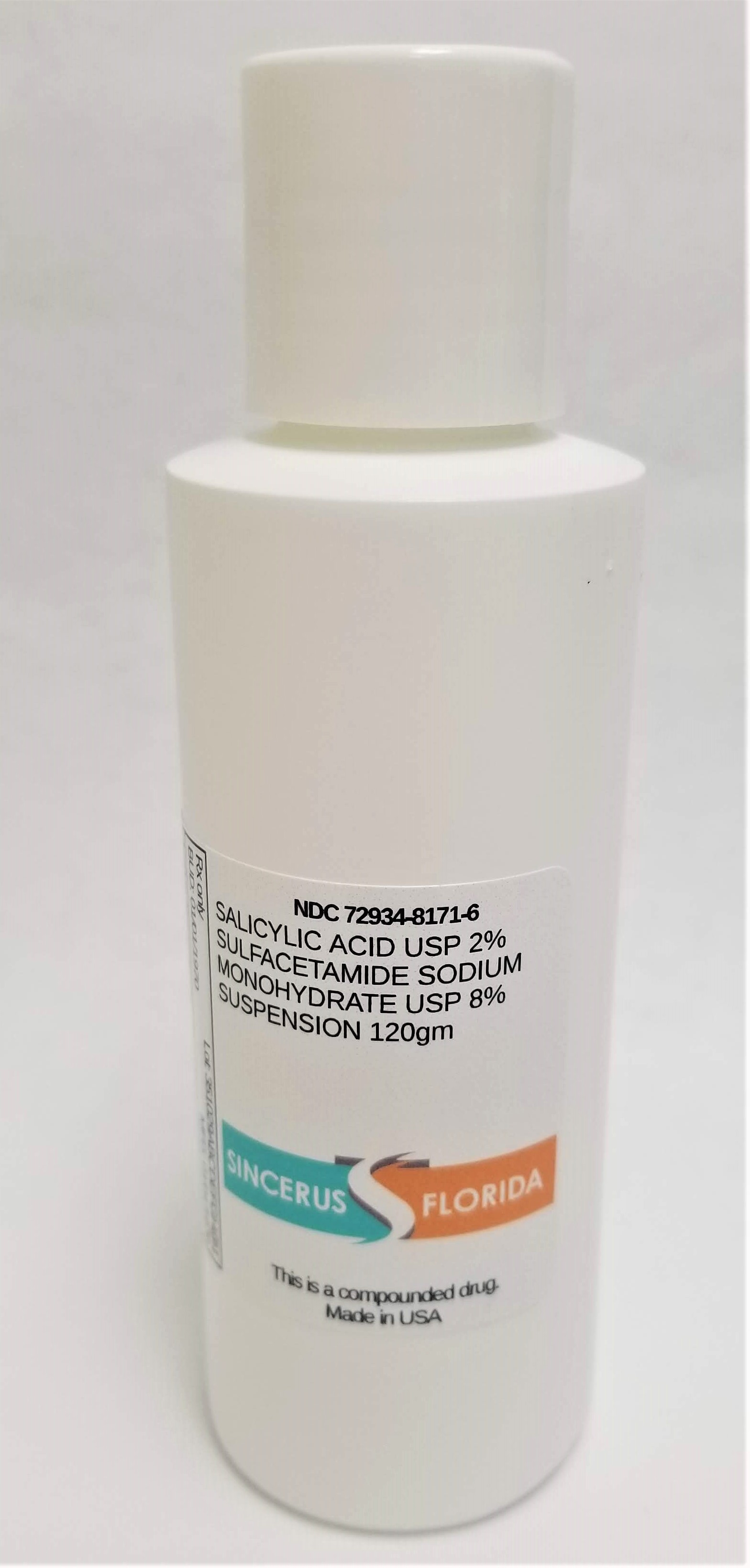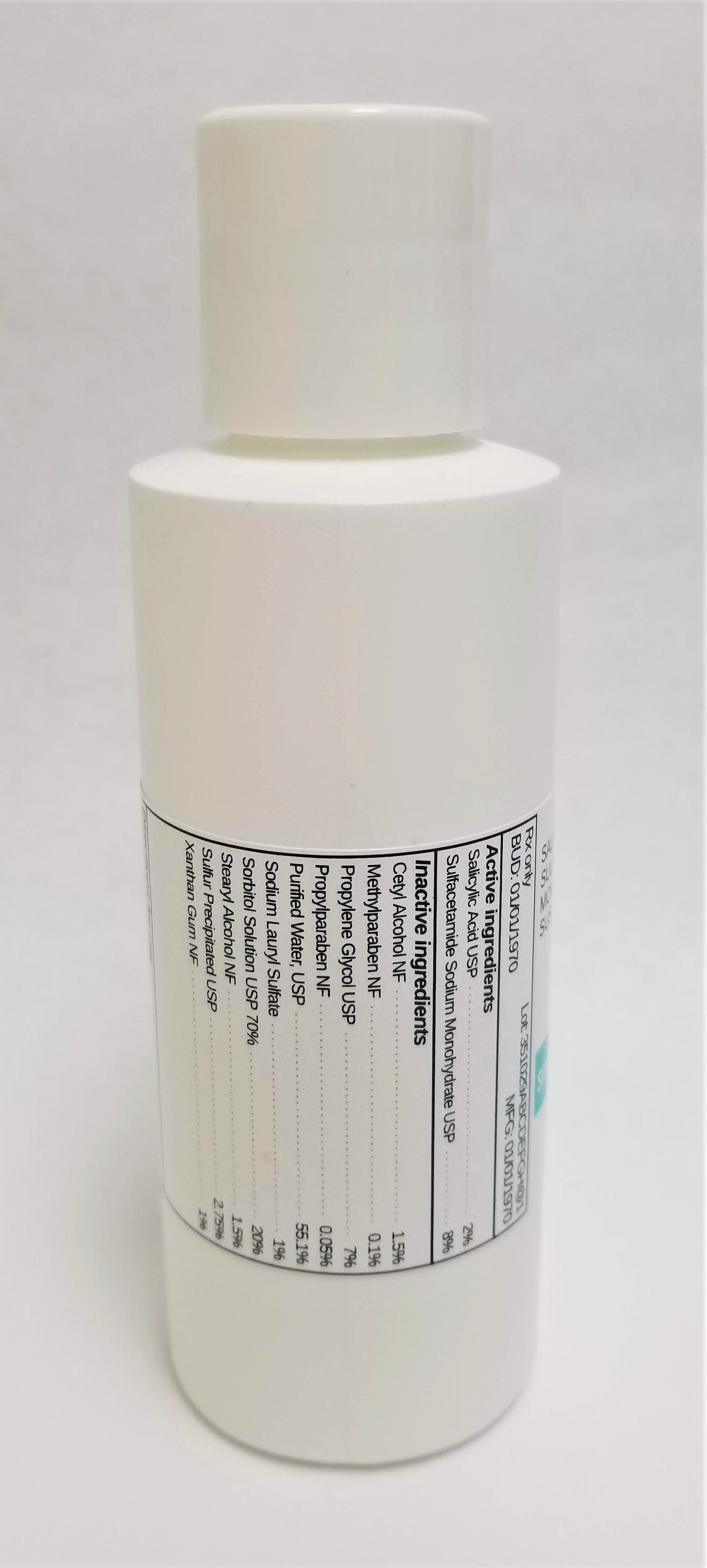 DRUG LABEL: SALICYLIC ACID 2% / SODIUM SULFACETAMIDE MONOHYDRATE 8%
NDC: 72934-8171 | Form: SUSPENSION
Manufacturer: Sincerus Florida, LLC
Category: prescription | Type: HUMAN PRESCRIPTION DRUG LABEL
Date: 20190516

ACTIVE INGREDIENTS: SULFACETAMIDE SODIUM 8 g/100 g; SALICYLIC ACID 2 g/100 g

SALICYLIC ACID 2% / SODIUM SULFACETAMIDE MONOHYDRATE 8%